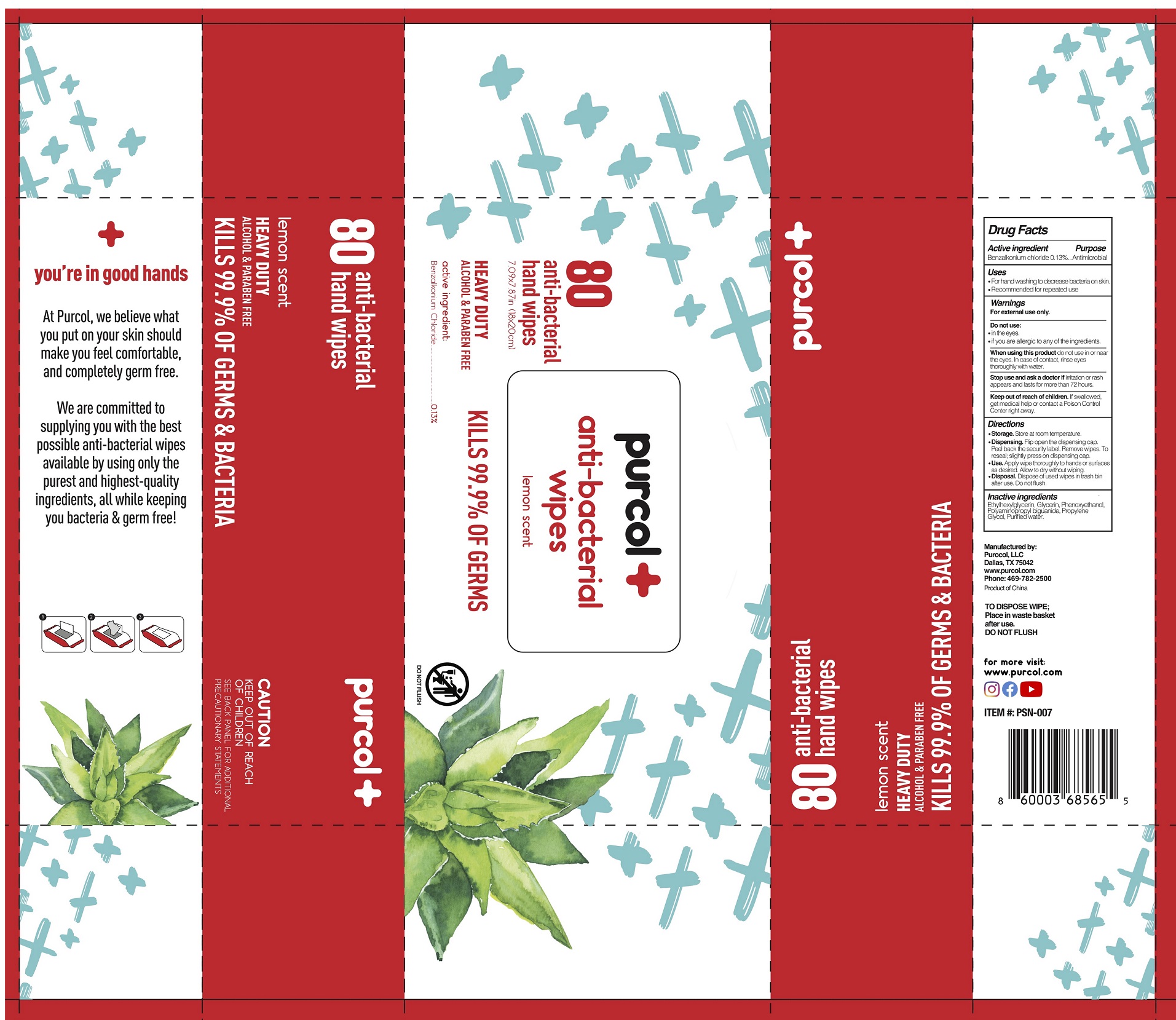 DRUG LABEL: Purcol Antibacterial Wipes Lemon Scent
NDC: 75266-001 | Form: CLOTH
Manufacturer: Purocol LLC
Category: otc | Type: HUMAN OTC DRUG LABEL
Date: 20210311

ACTIVE INGREDIENTS: BENZALKONIUM CHLORIDE 1.3 mg/1 mL
INACTIVE INGREDIENTS: ETHYLHEXYLGLYCERIN; GLYCERIN; PHENOXYETHANOL; POLYAMINOPROPYL BIGUANIDE; PROPYLENE GLYCOL; WATER

Purcol Anti-Bacterial Wipes Lemon Scent

Active ingredient

Benzalkonium chloride 0.13%

Purpose

Antimicrobial

Uses

- For hand washing to decrease bacteria on skin.
- Recommended for repeated use

Warnings

For external use only.

Do not use:

- in the eyes.
- if you are allergic to any of the ingredients.

When using this product

do not use in or near the eyes. In case of contact, rinse eyes thoroughly with water.

Stop use and ask a doctor if

irritation or rash appears and lasts for more than 72 hours.

Keep out of reach of children.

If swallowed, get medical help or contact Poison Control Center right away.

Directions

- Storage. Store at room temperature.
- Dispensing. Flip open the dispending cap. Peel back the security label. Remove wipes. To reseal: slightly press on dispensing cap.
- Use. Apply wipe thoroughly to hands or surfaces as desired. Allow to dry without wiping.
- Disposal. Dispose of used wipes in trash bin after use. Do not flush.

Inactive ingredients

Ethylhexylglycerin, Glycerin, Phenoxyethanol, Polyaminopropyl biguanide, Propylene Glycol, Purified water.